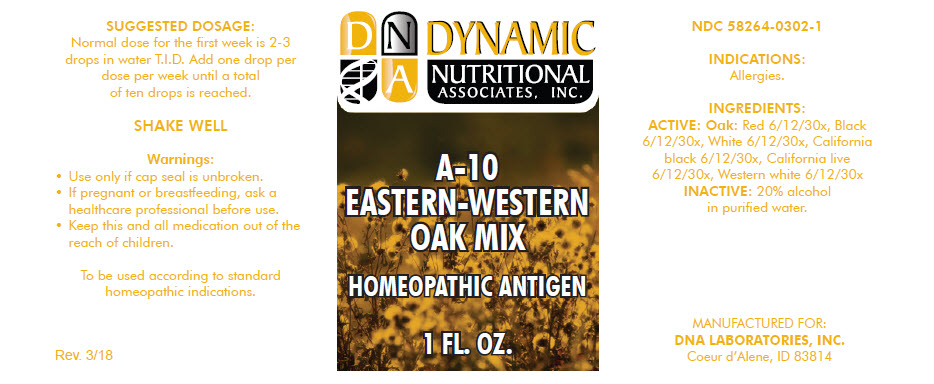 DRUG LABEL: A-10
NDC: 58264-0302 | Form: SOLUTION
Manufacturer: DNA Labs, Inc.
Category: homeopathic | Type: HUMAN OTC DRUG LABEL
Date: 20250109

ACTIVE INGREDIENTS: QUERCUS RUBRA WHOLE 30 [hp_X]/1 mL; QUERCUS VELUTINA WHOLE 30 [hp_X]/1 mL; QUERCUS ALBA WOOD 30 [hp_X]/1 mL; QUERCUS KELLOGGII WHOLE 30 [hp_X]/1 mL; QUERCUS AGRIFOLIA WHOLE 30 [hp_X]/1 mL; QUERCUS GARRYANA WHOLE 30 [hp_X]/1 mL
INACTIVE INGREDIENTS: ALCOHOL; WATER

A-10

NDC 58264-0302-1

INDICATIONS

PURPOSE

Allergies.

INGREDIENTS

ACTIVE

Oak

Red 6/12/30x, Black 6/12/30x, White 6/12/30x, California black 6/12/30x, California live 6/12/30x, Western white 6/12/30x

INACTIVE

20% alcohol in purified water.

SUGGESTED DOSAGE

Normal dose for the first week is 2-3 drops in water T.I.D. Add one drop per dose per week until a total of ten drops is reached.

STORAGE AND HANDLING

SHAKE WELL

Warnings

- Use only if cap seal is unbroken.

PREGNANCY OR BREAST FEEDING

- If pregnant or breastfeeding, ask a healthcare professional before use.

KEEP OUT OF REACH OF CHILDREN

- Keep this and all medication out of the reach of children.

To be used according to standard homeopathic indications.

PRINCIPAL DISPLAY PANEL - 1 FL. OZ. Bottle Label

DYNAMIC
NUTRITIONAL
ASSOCIATES, INC.

A-10
EASTERN-WESTERN
OAK MIX

HOMEOPATHIC ANTIGEN

1 FL. OZ.